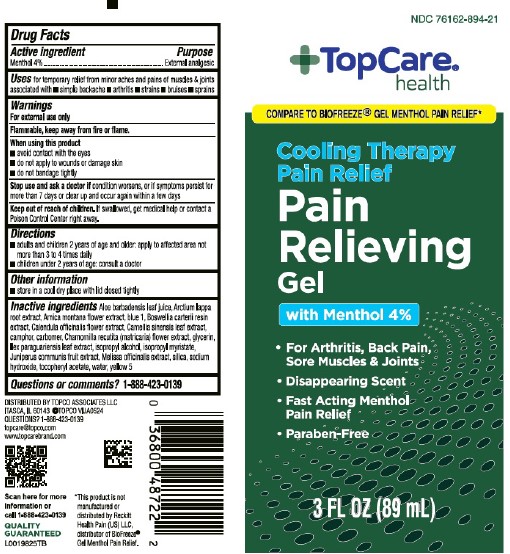 DRUG LABEL: Gel Cooling Pain Relief
NDC: 76162-894 | Form: GEL
Manufacturer: Topco Associates LLC
Category: otc | Type: HUMAN OTC DRUG LABEL
Date: 20260213

ACTIVE INGREDIENTS: MENTHOL 40 mg/1 mL
INACTIVE INGREDIENTS: ALOE VERA LEAF; ARCTIUM LAPPA ROOT; ARNICA MONTANA FLOWER; FD&C BLUE NO. 1; FRANKINCENSE; CALENDULA OFFICINALIS FLOWER; GREEN TEA LEAF; CAMPHOR (NATURAL); CARBOMER HOMOPOLYMER, UNSPECIFIED TYPE; CHAMOMILE; GLYCERIN; ILEX PARAGUARIENSIS LEAF; ISOPROPYL ALCOHOL; ISOPROPYL MYRISTATE; JUNIPER BERRY; MELISSA OFFICINALIS WHOLE; SILICON DIOXIDE; .ALPHA.-TOCOPHEROL ACETATE; TROLAMINE; WATER; FD&C YELLOW NO. 5

Top Care 894.002/894AB
Gel Cooling Pain Relief

Active ingredient

Menthol 4%

Purpose

External analgesic

Use

for temporary relief from minor aches and pains of muscles & joints associated with

- simple backache
- arthritis
- strains
- bruises
- sprains

Warnings

For external use only

Flammable, keep away from fire or flame.

When using this product

- avoid contact with the eyes
- do not apply to wounds or damaged skin
- do not bandage tightly

Stop use and ask a doctor if

condition worsens, or if symptoms persist for more than 7 days or clear up and occur again within a few days

Keep out of reach of children.

If swallowed, get medical help or contact a Poison Control Center right away.

Directions

- adults and children 2 years of age and older: apply to affected area not more than 3 to 4 times daily
- children under 2 years of age: consult a doctor

Other information

- store in a cool dry place with lid closed tightly

Inactive ingredients

Aloe barbadensis leaf juice, Arctium lappa root extract, Arnica montana flower extract, blue 1, Boswellia carterii resin extract, Calendula officinalis flower extract, Camellia sinensis leaf extract, camphor, carbomer, Chamomilla recutita (matricaria) flower extract, glycerin, llex paraguariensis leaf extract, isopropyl alcohol, isopropyl myristate, Juniperus communis fruit extract, Melissa officinalis extract, silica, sodium hydroxide, tocopheryl acetate, water, yellow 5

Questions or comments?

1-888-423-0139

Adverse Reactions Section

DISTRIBUTED BY TOPCO ASSOCIATES LLC

ITASCA, IL 60143 ©TOPCO VIJA 0524

QUESTIONS? 1-888-423-0139

topcare@topco.com

www.topcarebrand.com

Scan here for more information or call 1-888-423-0139

QUALITY GUARANTEED

Disclaimer

*This products is not manufactured or distributed by Reckitt Health Pain (US) LLC, distributor of BioFreeze® Gel Menthol Pain Relief.

Principal display panel

NDC 76162-894-21

TopCare® health

COMPARE TO BIOFREEZE®GEL MENTHOL PAIN RELIEF*

Cooling Therapy Pain Relief

Pain Relieving Gel

with Menthol 4%

- For Arthritis, Back Pain, Sore Muscles & Joints
- Disappearing Scent
- Fast Acting Menthol Pain Relief
- Paraben-Free

3 FL OZ (89 mL)